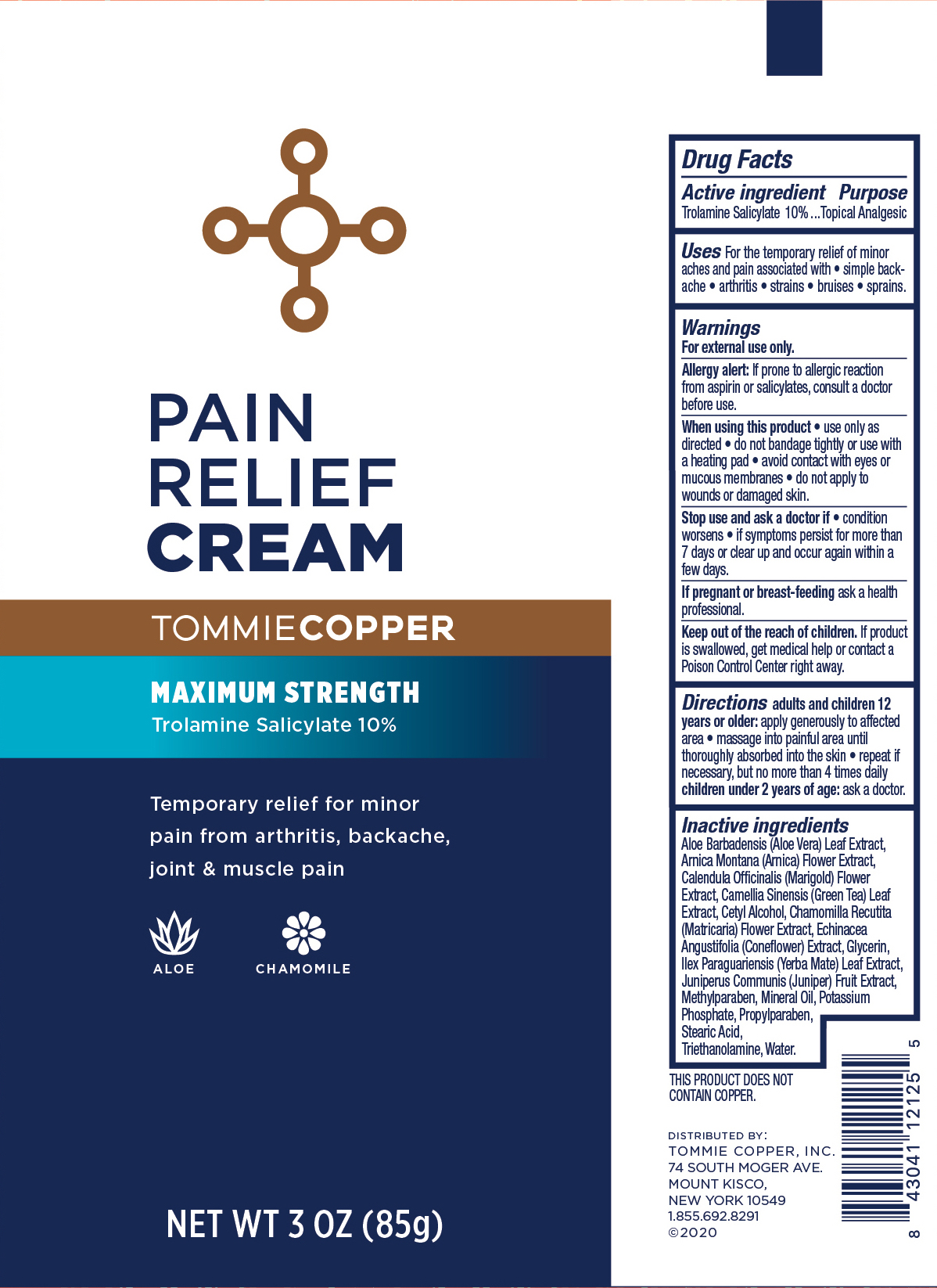 DRUG LABEL: Tommie Copper Pain Relief
NDC: 72562-103 | Form: CREAM
Manufacturer: Tommie Copper, Inc.
Category: otc | Type: HUMAN OTC DRUG LABEL
Date: 20241215

ACTIVE INGREDIENTS: TROLAMINE SALICYLATE 10 g/100 g
INACTIVE INGREDIENTS: CALENDULA OFFICINALIS FLOWER; ILEX PARAGUARIENSIS LEAF; JUNIPER BERRY; CHAMOMILE; ECHINACEA ANGUSTIFOLIA; STEARIC ACID; CETYL ALCOHOL; WATER; GLYCERIN; TROLAMINE; METHYLPARABEN; MINERAL OIL; POTASSIUM PHOSPHATE, MONOBASIC; PROPYLPARABEN; ALOE VERA LEAF; GREEN TEA LEAF; ARNICA MONTANA FLOWER

Pain Relief Cream, Trolamine Salicylate 10%

ACTIVE INGREDIENT

Trolamine Salicylate 10%

PURPOSE

Topical Analgesic.

DOSAGE AND ADMINISTRATION

For the temporary relief of minor aches and pain associated with simple backache, arthritis, strains, bruises, and sprains.

WARNINGS

For external use only.

Allergy Alert: if prone to allergic reaction from aspirin or salicylates, consult a doctor before use.

When using this product use only as directed, avoid taking a bath or shower within 1 hour before or after applying, do not bandage or use with a heating pad, avoid contact with eyes or mucous membranes, do not apply to wounds or damaged skin.

Stop use and ask a doctor if condition worsens or symptoms persist for more than 7 days, if symptoms clear up and occur again within a few days.

PREGNANCY OR BREAST FEEDING

If pregnant or breast-feeding, ask a health care professional before use.

Keep out of reach of children.

INDICATIONS AND USAGE

Adults and children 12 years of age: apply generously to the affected area, massage into painful area until thoroughly absorbed into the skin, repeat as necessary, but not more than 3 to 4 times daily. Children under 12 years of age: ask a doctor.

INACTIVE INGREDIENT

Aloe Barbadensis (Aloe Vera) Leaf Extract, Arnica Montana (Arnica) Flower Extract, Calendula Officinalis (Marigold) Flower Extract, Camellia Sinensis (Green Tea) Leaf Extract, Cetyl Alcohol, Chamomilla Recutita (Matricaria) Flower Extract, Echinacea Angustifolia (Coneflower) Extract, Glycerin, Ilex Paraguariensis (Yerba Mate) Leaf Extract, Juniperus Communis (Juniper) Fruit Extract, Methylparaben, Mineral Oil, Potassium Phosphate, Propylparaben, Stearic Acid, Triethanolamine, Water.